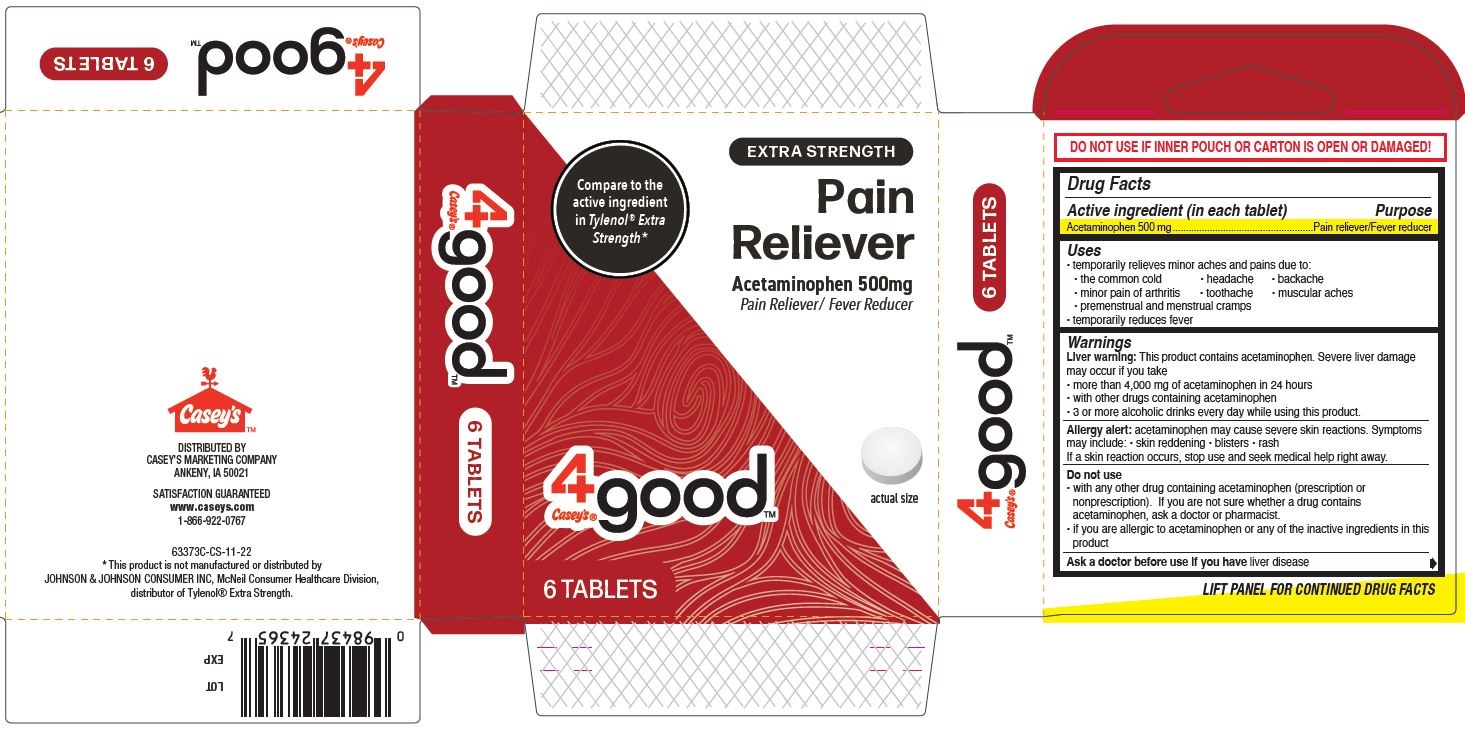 DRUG LABEL: Pain Reliever, Caseys 4good
NDC: 66715-6337 | Form: TABLET
Manufacturer: Lil' Drug Store Products, Inc.
Category: otc | Type: HUMAN OTC DRUG LABEL
Date: 20241216

ACTIVE INGREDIENTS: ACETAMINOPHEN 500 mg/1 1
INACTIVE INGREDIENTS: STARCH, CORN; POVIDONE; TITANIUM DIOXIDE; HYPROMELLOSE, UNSPECIFIED; SODIUM STARCH GLYCOLATE TYPE A CORN; STEARIC ACID; POLYETHYLENE GLYCOL, UNSPECIFIED

Pain Reliever, 6ct, Casey's 4goodTM

Drug Facts

Active ingredient

Active ingredient (in each tablet)

Acetaminophen 500 mg

Purpose

Pain reliever/Fever reducer

Uses

- temporarily relieves minor aches and pains due to:
- the common cold
- headache
- backache
- minor pain of arthritis
- toothache
- muscular aches
- premenstrual and menstrual cramps
- temporarily reduces fever

Warnings

Liver warning

Liver warning: This product contains acetaminophen. Severe liver damage may occur if you take

- more than 4,000 mg of acetaminophen in 24 hours
- with other drugs containing acetaminophen
- 3 or more alcoholic drinks every day while using this product.

Allergy alert

Allergy alert: acetaminophen may cause severe skin reactions. Symptomsmay include:

- skin reddening
- blisters
- rash

If a skin reaction occurs, stop use and seek medical help right away.

Do not use

- with any other drug containing acetaminophen (prescription or nonprescription). If you are not sure whether a drug contains

acetaminophen, ask a doctor or pharmacist.

- if you are allergic to acetaminophen or any of the inactive ingredients in this product

Ask a doctor before use if you have liver disease

Ask a doctor or pharmacist before use if you are taking the blood thinning drug warfarin

Stop use and ask a doctor if

- pain gets worse or lasts for more than 10 days
- fever gets worse or lasts for more than 3 days
- new symptoms appear
- redness or swelling is present

These could be signs of a serious condition.

If pregnant or breast-feeding, ask a health professional before use.

Keep out of reach of children

Overdose warning

Overdose warning: Taking more than the recommended dose (overdose) may cause liver damage. In case of overdose, get medical help or contact a Poison Control Center (1-800-222-1222) right away. Quick medical attention is critical for adults as well as for children even if you do not notice any signs or symptoms.

Directions

- do not take more than directed (see Overdose warning)

adults and children 12 years and over | - take 2 tablets every 6 hours while symptoms last - do not take more than 6 tablets in 24 hours, unless directed by a doctor - do not use for more than 10 days unless directed by a doctor
12 years and over | ask a doctor

Other information

- store at 59-86˚F (15-30˚C)

Inactive ingredients

corn starch, hypromellose, polyethylene glycol, povidone, sodium starch glycolate, stearic acid, titanium dioxide

Questions or comments?

call toll-free 1-877-507-6516 (M-F 8AM-4:30PM CST)

Pain Reliever, 6ct Casey's 4good PDP/Packge

Compare to the
active ingredient
in Tylenol® Extra
Strength*

EXTRA STRENGTH

Pain

Reliever

Acetaminophen 500 mg

Pain Reliever/Fever Reducer

[Casey;s 4good logo]

[tablet image]

actual size

6 TABLETS